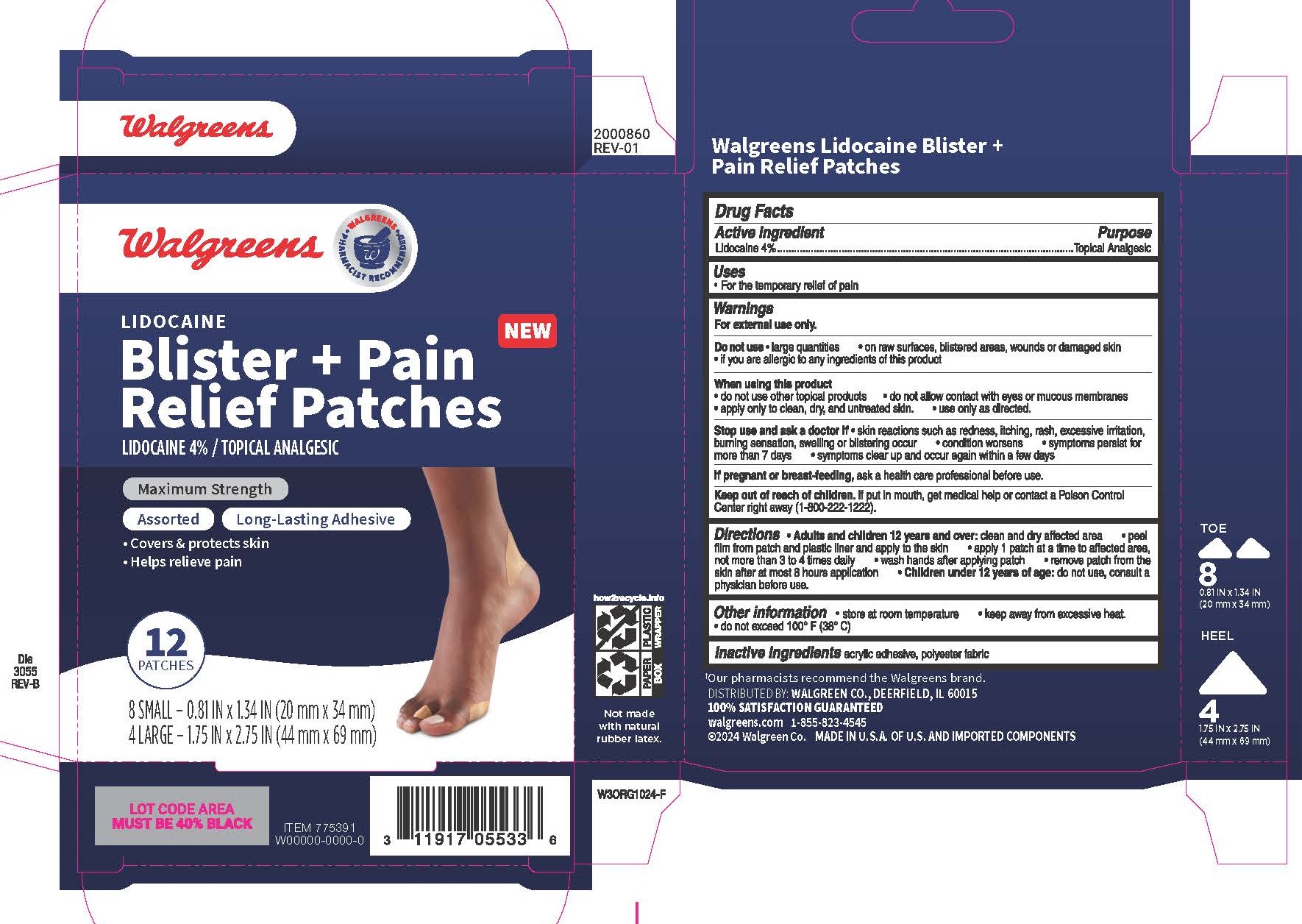 DRUG LABEL: Walgreens
NDC: 0363-1002 | Form: PATCH
Manufacturer: WALGREENS
Category: otc | Type: HUMAN OTC DRUG LABEL
Date: 20241022

ACTIVE INGREDIENTS: LIDOCAINE 4 mg/100 mg
INACTIVE INGREDIENTS: ETHYLENE-VINYL ACETATE COPOLYMER (15% VINYL ACETATE)

Lidocaine Blister + Pain Relief Patches

Active ingredient

Lidocaine 4%

Purpose

Topical Analgesic

Uses

- For the temporary relief of pain

Warnings

For external use only

Do not use

- large quantities
- on raw surfaces, blistered areas, wounds or damaged skin
- if you are allergic to any ingredients of this product

When using this product

- do not use other topical products
- do not allow contact with eyes or mucous membranes
- apply only to clean, dry, and untreated skin
- use only as directed

Stop use and ask a doctor if

- skin reactions such as redness, itching, rash, excessive irritation, burning sensation, swelling or blistering occur
- condition worsens
- symptoms persist for more than 7 days
- symptoms clear up and occur again within a few days

If pregnant or breast-feeding

ask a health care professional before use.

Keep out of reach of children.

If put in mouth, get medical help or contact a Poison Control Center right away (1-800-222-1222).

Directions

- Adults and children 12 years and over: clean and dry affected area
- peel film from patch and plastic liner and apply to the skin
- apply 1 patch at a time to affected area, not more than 3 to 4 times daily
- wash hands after applying patch
- remove patch from the skin after at most 8 hours application
- Children under 12 years of age: do not use, consult a physician before use.

Other information

- Store at room temperature
- keep away from excessive heat
- do not exceed 100oF (38oC)

Inactive ingredients

acrylic adhesive, polyester fabric

Principal Display Panel

Walgreens

LIDOCAINE

Blister + Pain Relief Patches

LIDOCAINE 4% / TOPICAL ANALGESIC

Maximum Strength

Assorted Long-Lasting Adhesive

- Covers & protects skin
- Helps relieve pain

12 PATCHES

8 SMALL - 0.81 IN x 1.34 IN (20 mm x 34 mm)

4 LARGE - 1.75 IN x 2.75 IN (44 mm x 69 mm)